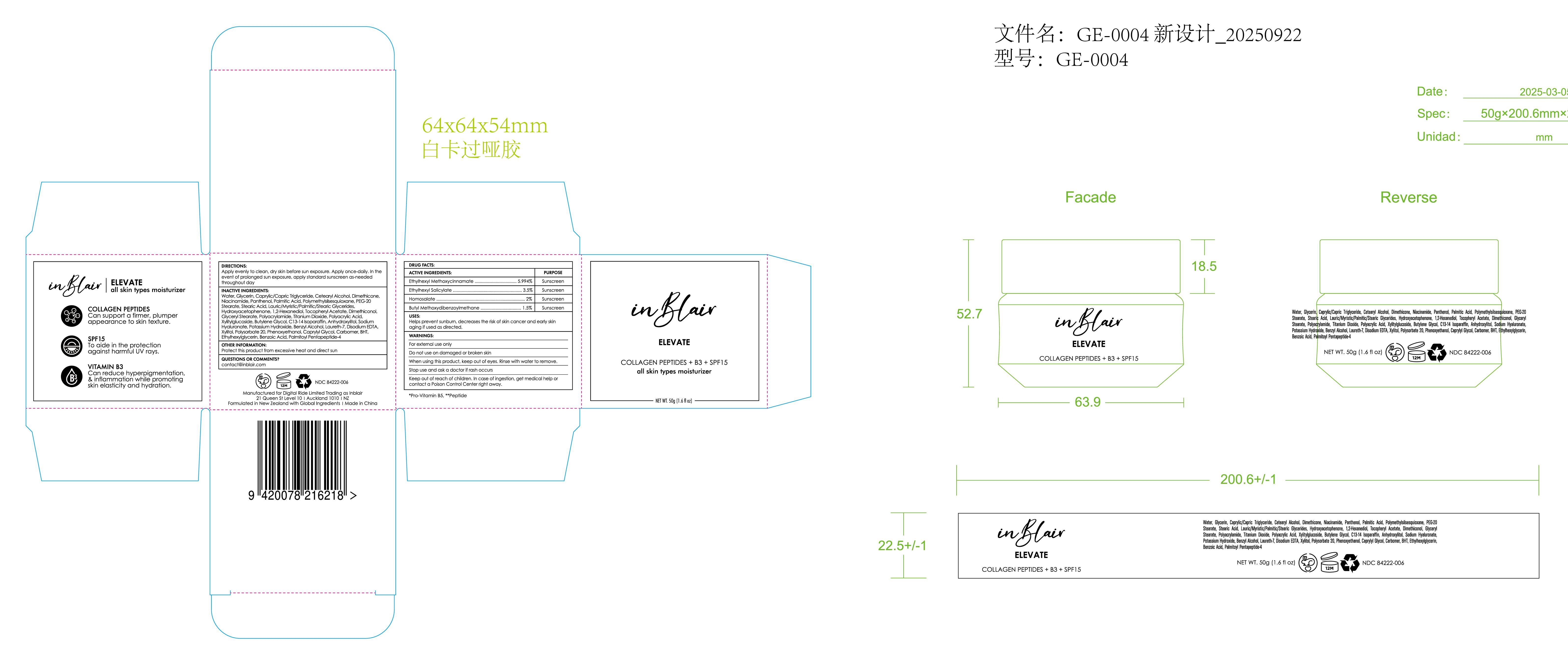 DRUG LABEL: inblair Moisturizer SPF 15
NDC: 84222-006 | Form: CREAM
Manufacturer: Foshan Miwei Cosmetics Co.,Ltd.
Category: otc | Type: HUMAN OTC DRUG LABEL
Date: 20250928

ACTIVE INGREDIENTS: ETHYLHEXYL SALICYLATE 3.5 g/100 mL; HOMOSALATE 2 g/100 mL; BUTYL METHOXYDIBENZOYLMETHANE 1.5 g/100 mL; ETHYLHEXYL METHOXYCINNAMATE 5.994 g/100 mL
INACTIVE INGREDIENTS: LAURIC/MYRISTIC/PALMITIC/STEARIC GLYCERIDES 0.55 mL/100 mL; POLYSORBATE 20 0.025 mL/100 mL; PANTHENOL 2 mL/100 mL; BENZOIC ACID 0.002 mL/100 mL; WATER 46.918 mL/100 mL; GLYCERIN 11.34935 mL/100 mL; BENZYL ALCOHOL 0.083 mL/100 mL; PHENOXYETHANOL 0.015 mL/100 mL; PALMITOYL PENTAPEPTIDE-4 0.00065 mL/100 mL; POLYACRYLAMIDE (10000 MW) 0.315 mL/100 mL; CETEARYL ALCOHOL 4.25 mL/100 mL; POTASSIUM HYDROXIDE 0.1 mL/100 mL; BHT 0.006 mL/100 mL; ANHYDROXYLITOL 0.12 mL/100 mL; SODIUM HYALURONATE 0.1 mL/100 mL; LAURETH-7 0.072 mL/100 mL; POLYMETHYLSILSESQUIOXANE (4.5 MICRONS) 1 mL/100 mL; PEG-20 STEARATE 0.75 mL/100 mL; TITANIUM DIOXIDE 0.3 mL/100 mL; DIMETHICONOL (40 CST) 0.4 mL/100 mL; CAPRYLIC/CAPRIC TRIGLYCERIDE 8 mL/100 mL; POLYACRYLIC ACID (250000 MW) 0.3 mL/100 mL; XYLITYLGLUCOSIDE 0.25 mL/100 mL; CAPRYLYL GLYCOL 0.01275 mL/100 mL; NIACINAMIDE 2 mL/100 mL; HYDROXYACETOPHENONE 0.5 mL/100 mL; DIMETHICONE 3.6 mL/100 mL; CARBOMER 0.01 mL/100 mL; GLYCERYL STEARATE 0.4 mL/100 mL; EDETATE DISODIUM 0.05 mL/100 mL; XYLITOL 0.05 mL/100 mL; C13-14 ISOPARAFFIN 0.225 mL/100 mL; ETHYLHEXYLGLYCERIN 0.00225 mL/100 mL; STEARIC ACID 0.7 mL/100 mL; BUTYLENE GLYCOL 0.25 mL/100 mL; 1,2-HEXANEDIOL 0.5 mL/100 mL; .ALPHA.-TOCOPHEROL ACETATE 0.5 mL/100 mL; PALMITIC ACID 1.3 mL/100 mL

inblair Moisturizer SPF 15

Drug Facts

ACTIVE INGREDIENTS PURPOSE

Ethylhexyl Methoxycinnamate 5.994%..............................................Sunscreen

Ethylhexyl Salicylate 3.5%................................................................ Sunscreen

Homosalate 2%................................................................................. Sunscreen

Butyl Methoxydibenzoylmethane 1.5%............................................. Sunscreen

PURPOSE

Sunscreen

Uses:

Helps prevent sunburn, decreases the risk of skin cancer and early skin aging if used as directed.

WARNINGS

For external use only

Do not use on damaged or broken skin

When using this product, keep out of eyes. Rinse with water to remove.

Stop use and ask a doctor if rash occurs

Keep out of reach of children. In case of ingestion, get medical help or

contact a Poison Control Center right away.

Keep out of reach of children. In case of ingestion, get medical help or contact a Poison Control Center right away.

DOSAGE AND ADMINISTRATION

Apply evenly to clean, dry skin before sun exposure. Apply once-daily. In the

event of prolonged sun exposure, apply standard sunscreen as-needed

throughout day

INACTIVE INGREDIENT

Water, Glycerin, Caprylic/Capric Triglyceride, Cetearyl Alcohol, Dimethicone, Niacinamide, Panthenol, Palmitic Acid, Polymethylsilsesquioxane, PEG-20 Stearate, Stearic Acid, Lauric/Myristic/Palmitic/Stearic Glycerides, Hydroxyacetophenone, 1,2-Hexanediol, Tocopheryl Acetate, Dimethiconol, Glyceryl Stearate, Polyacrylamide, Titanium Dioxide, Polyacrylic Acid, Xylitylglucoside, Butylene Glycol, C13-14 Isoparaffin, Anhydroxylitol, Sodium Hyaluronate, Potassium Hydroxide, Benzyl Alcohol, Laureth-7, Disodium EDTA, Xylitol, Polysorbate 20, Phenoxyethanol, Caprylyl Glycol, Carbomer, BHT, Ethylhexylglycerin, Benzoic Acid, Palmitoyl Pentapeptide-4

OTHER SAFETY INFORMATION

inblair

ELEVATE

COLLAGEN PEPTIDES + B3 + SPF15

all skin types moisturizer

NET WT.50g[1.6fl oz]

Drug Facts

ACTIVE INGREDIENTS PURPOSE

Ethylhexyl Methoxycinnamate 5.994%................................................. Sunscreen

Ethylhexyl Salicylate 3.5%................................................................ Sunscreen

Homosalate 2%................................................................................. Sunscreen

Butyl Methoxydibenzoylmethane 1.5%............................................. Sunscreen

Uses:

Helps prevent sunburn, decreases the risk of skin cancer and early skin aging if used as directed.

WARNINGS:

For external use only

Do not use on damaged or broken skin

When using this product, keep out of eyes. Rinse with water to remove.

Stop use and ask a doctor if rash occurs

Keep out of reach of children. In case of ingestion, get medical help or

contact a Poison Control Center right away.

*Pro-Vitamin B5, **Peptide

DIRECTIONS:

Apply evenly to clean, dry skin before sun exposure. Apply once-daily. In the

event of prolonged sun exposure, apply standard sunscreen as-needed

throughout day

INACTIVE INGREDIENTS:

Water, Glycerin, Caprylic/Capric Triglyceride, Cetearyl Alcohol, Dimethicone, Niacinamide, Panthenol, Palmitic Acid, Polymethylsilsesquioxane, PEG-20 Stearate, Stearic Acid, Lauric/Myristic/Palmitic/Stearic Glycerides, Hydroxyacetophenone, 1,2-Hexanediol, Tocopheryl Acetate, Dimethiconol, Glyceryl Stearate, Polyacrylamide, Titanium Dioxide, Polyacrylic Acid, Xylitylglucoside, Butylene Glycol, C13-14 Isoparaffin, Anhydroxylitol, Sodium Hyaluronate, Potassium Hydroxide, Benzyl Alcohol, Laureth-7, Disodium EDTA, Xylitol, Polysorbate 20, Phenoxyethanol, Caprylyl Glycol, Carbomer, BHT, Ethylhexylglycerin, Benzoic Acid, Palmitoyl Pentapeptide-4.

OTHER INFORMATION:

Protect this product from excessive heat and direct sun

QUESTIONS OR COMMENTS?

contact@inblair.com

Manufactured for Digital Ride Limited Trading as Inblair

21 Queen St Level 10 I Auckland 1010 INZ

Formulated in New Zealand with Global Ingredients I Made in China

Inblair ELEVATE

all skin types moisturizer

COLLAGEN PEPTIDES

Can support a firmer, plumper

appearance to skin texture.

SPF15

To aide in the protection

against harmful UV rays.

VITAMIN B3

Can reduce hyperpigmentation,

& inflammation while promoting

skin elasticity and hydration.

Uses:

Helps prevent sunburn, decreases the risk of skin cancer and early skin aging if used as directed.

DIRECTIONS:

Apply evenly to clean, dry skin before sun exposure. Apply once-daily. In the

event of prolonged sun exposure, apply standard sunscreen as-needed

throughout day